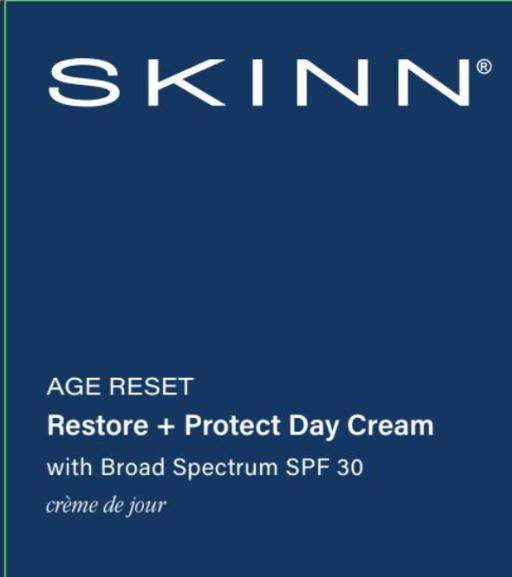 DRUG LABEL: AGE RESET Restore Plus Protect Day Cream
NDC: 76286-101 | Form: LOTION
Manufacturer: SKINN COSMETICS, LLC
Category: otc | Type: HUMAN OTC DRUG LABEL
Date: 20260115

ACTIVE INGREDIENTS: ZINC OXIDE 10 g/100 mL
INACTIVE INGREDIENTS: TRIETHOXYCAPRYLYLSILANE; CAPRYLIC/CAPRIC TRIGLYCERIDE; SORBITAN OLIVATE; TOCOPHEROL; SODIUM LACTATE; GLYCERIN; ASCORBIC ACID; PALMITOYL TRIPEPTIDE-1; CI 77491; CI 77492; CI 77499; CARBOMER; POLYSORBATE 20; TERMINALIA CHEBULA FRUIT; PALMITOYL TETRAPEPTIDE-7; BUTYLENE GLYCOL; ETHYLHEXYLGLYCERIN; WATER; DIMETHICONE; CETEARYL ALCOHOL; CETEARYL OLIVATE; POLYGLYCERYL-3 DIISOSTEARATE; CETEARYL GLUCOSIDE; PHENOXYETHANOL; XANTHAN GUM

SKINN (as PLD): AGE RESET Restore + Protect Day Cream (76286-101)

ACTIVE INGREDIENT

ZINC OXIDE 10%

PURPOSE

SUNSCREEN

USE

HELPS PREVENT SUNBURN

WARNINGS

- FOR EXTERNAL USE ONLY.
- DO NOT USE ON DAMAGED OR BROKEN SKIN.
- WHEN USING THIS PRODUCT KEEP OUT OF EYES. RINSE WITH WATER TO REMOVE.
- STOP USE AND ASK A DOCTOR IF RASH OCCURS.

KEEP OUT OF REACH OF CHILDREN. IF SWALLOWED, GET MEDICAL HELP OR CONTACT A POISON CONTROL CENTER RIGHT AWAY.

DIRECTIONS

- APPLY LIBERALLY 15 MINUTES BEFORE SUN EXPOSURE.
- CHILDREN UNDER 6 MONTHS OF AGE: ASK A DOCTOR.
- USE A WATER-RESISTANT SUNSCREEN IF SWIMMING OR SWEATING.
- REAPPLY AT LEAST EVERY 2 HOURS.
- SUNPROTECTION MEASURES: SPENDING TIME IN THE SUN INCREASES YOUR RISK OF SKIN CANCER AND EARLY AGING. TO DECREASE THE RISK, REGULARLY USE A BROAD SPECTRUM SPF VALUE OF 15 OR HIGHER AND OTHER SUN PROTECTION MEASURES INCLUDING:
- LIMIT TIME IN THE SUN, ESPECIALLY FROM 10 A.M. - 2 P.M.
- WEAR LONG-SLEEVED SHIRTS, PANTS, HATS, AND SUNGLASSES.

OTHER INFORMATION

- PROTECT THE PRODUCT IN THIS CONTAINER FROM EXCESSIVE HEAT AND DIRECT SUN.

INACTIVE INGREDIENTS

Water (Aqua), Butylene Glycol, Dimethicone, Caprylic/Capric Triglyceride, Cetearyl Alcohol, Cetearyl Olivate, Polyglyceryl-3 Diisostearate, Sorbitan Olivate, Terminalia Chebula Fruit Extract, Ascorbic Acid, Tocopherol, Palmitoyl Tripeptide-1, Palmitoyl Tetrapeptide-7, Glycerin, Sodium Lactate, Cetearyl Glucoside, Xanthan Gum, Polysorbate 20, Carbomer, Triethoxycaprylylsilane, Phenoxyethanol, Ethylhexylglycerin, Iron Oxides.